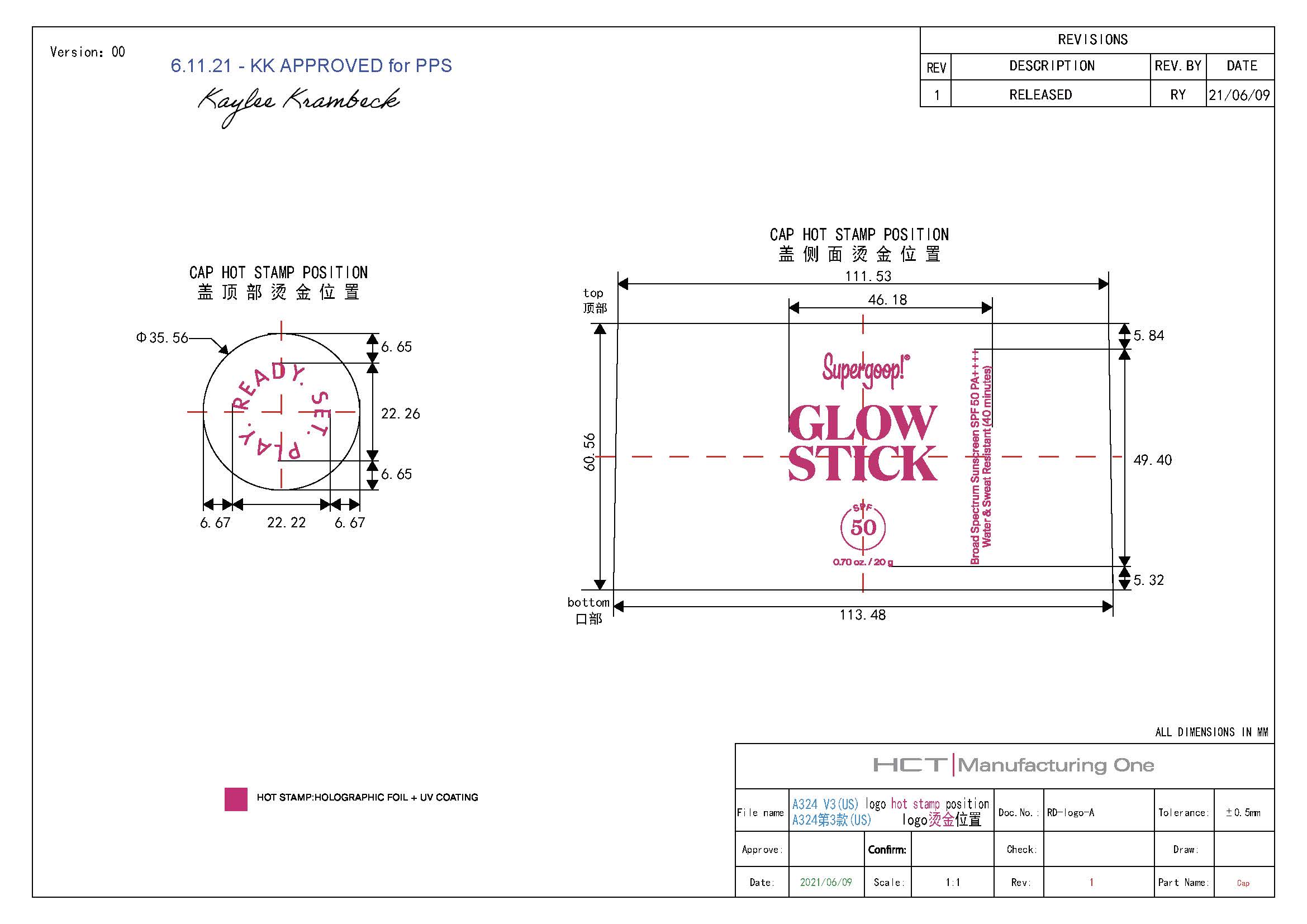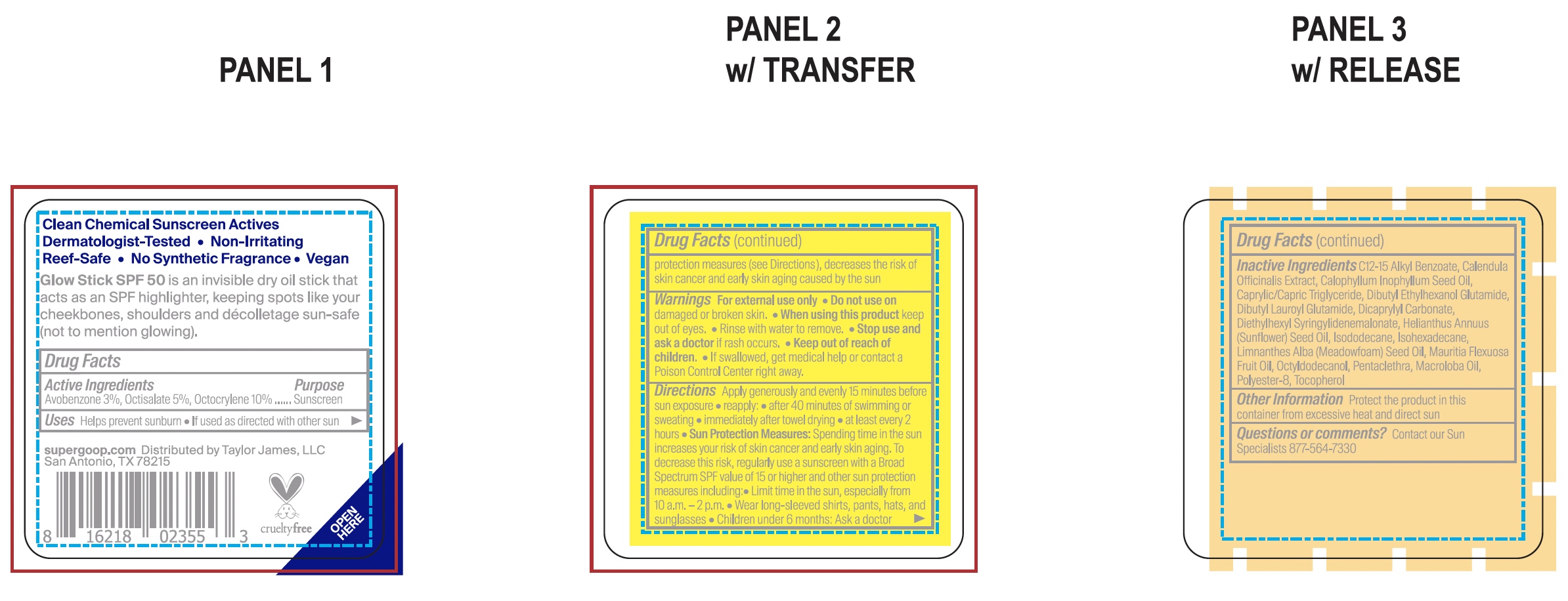 DRUG LABEL: Glow Stick Broad Spectrum SPF 50
NDC: 75936-157 | Form: STICK
Manufacturer: Taylor James Ltd.
Category: otc | Type: HUMAN OTC DRUG LABEL
Date: 20211027

ACTIVE INGREDIENTS: OCTISALATE 5 g/100 g; OCTOCRYLENE 10 g/100 g; AVOBENZONE 3 g/100 g
INACTIVE INGREDIENTS: MEADOWFOAM SEED OIL; MAURITIA FLEXUOSA FRUIT OIL; OCTYLDODECANOL; DIETHYLHEXYL SYRINGYLIDENEMALONATE; DIBUTYL ETHYLHEXANOYL GLUTAMIDE; DIBUTYL LAUROYL GLUTAMIDE; DICAPRYLYL CARBONATE; ALKYL (C12-15) BENZOATE; POLYESTER-8 (1400 MW, CYANODIPHENYLPROPENOYL CAPPED); TAMANU OIL; TOCOPHEROL; MEDIUM-CHAIN TRIGLYCERIDES; SUNFLOWER OIL; ISODODECANE; ISOHEXADECANE; CALENDULA OFFICINALIS FLOWER

Glow Stick Broad Spectrum SPF 50

Active Ingredients Purpose

Avobenzone 3% Sunscreen

Octisalate 5% Sunscreen

Octocrylene 10% Sunscreen

Uses

Helps prevent sunburn

If used as directed with other sun protection measures (see Directions), decreases the risk of skin cancer and early skin aging caused by the sun.

Keep out of reach of children. If product is swallowed, get medical help or contact a Poison Control Center right away.

Stop use and ask a doctor if rash occurs.

Warnings

For external use only

Do not use on damaged or broken skin

When using this product keep out of eyes. Rinse with water to remove.

Directions

- Apply generously and evenly 15 minutes before sun exposure
- Use a water-resistant sunscreen if swimming or sweating
- Reapply at least every 2 hours.
- Sun Protection Measures Spending time in the sun increases your risk of

skin cancer and early skin aging. To decrease this risk, regularly use a
sunscreen with a Broad-Spectrum SPF value of 15 or higher and other sun
protection measures including:

• limit your time in the sun, especially from 10
a.m. – 2 p.m.

• wear long-sleeved shirts, pants, hats, and sunglasses

•Children under 6 months of age: ask a doctor.

Inactive ingredients

C12-15 Alkyl Benzoate, Calendula Officinalis Extract, Calophyllum Inophyllum Seed Oil, Caprylic/Capric Triglyceride, Dibutyl Ethylhexanol Glutamide, Dibutyl Lauroyl Glutamide, Dicaprylyl Carbonate, Diethylhexyl Syringylidenemalonate, Helianthus Annuus (Sunflower) Oil, Isododecane, Isohexadecane, Limnanthes Alba (Meadowfoam) Seed Oil, Maurita Flexuosa Fruit Oil, Octyldodecanol, Pentaclethra, Macroloba Oil, Polyester-8, Tocopherol

PACKAGE LABEL

Supergoop!

Glow Stick Sunscreen

SPF 50

1.23 oz./ 35 g